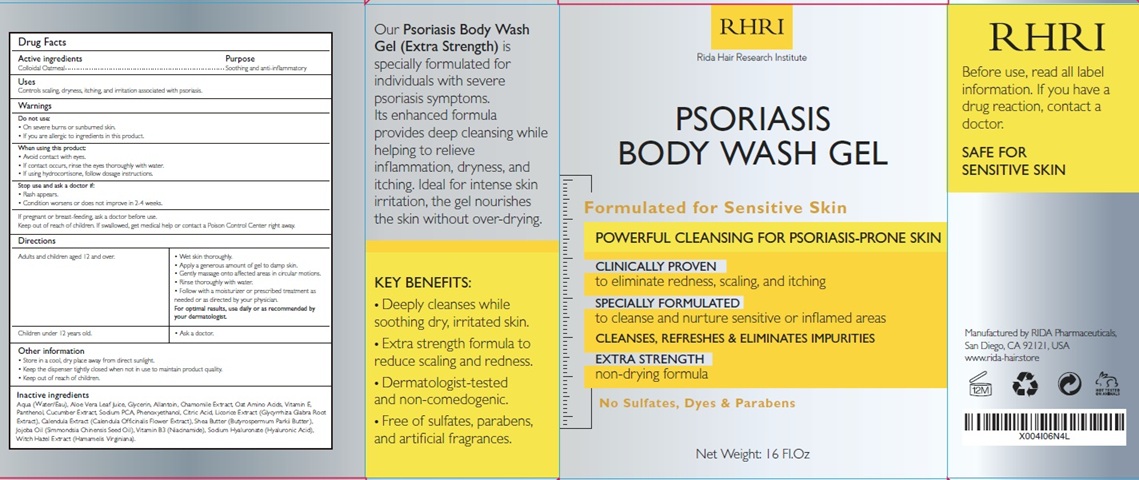 DRUG LABEL: Psoriasis Body Wash
NDC: 83004-027 | Form: GEL
Manufacturer: Rida LLC
Category: otc | Type: HUMAN OTC DRUG LABEL
Date: 20250603

ACTIVE INGREDIENTS: OATMEAL 5 g/100 mL
INACTIVE INGREDIENTS: WATER; ALOE VERA LEAF JUICE; GLYCERIN; ALLANTOIN; CHAMOMILE; AMINO ACIDS, OAT; TOCOPHEROL; PANTHENOL; CUCUMBER; SODIUM PYRROLIDONE CARBOXYLATE; PHENOXYETHANOL; CITRIC ACID MONOHYDRATE; GLYCYRRHIZA GLABRA (LICORICE) ROOT POWDER; CALENDULA OFFICINALIS FLOWER; SHEA BUTTER; JOJOBA OIL; NIACINAMIDE; HYALURONATE SODIUM; WITCH HAZEL

Active Ingredient

Colloidal Oatmeal 5%

Purpose

Soothing and anti-inflammatory

Uses

Controls scaling, dryness, itching, and irritation associated with psoriasis.

Warnings

Do not use:
• On severe burns or sunburned skin.
• If you are allergic to ingredients in this product.

When using this product:
• Avoid contact with eyes.
• If contact occurs, rinse the eyes thoroughly with water.
• If using hydrocortisone, follow dosage instructions.

Stop use and ask a doctor if:
• Rash appears.
• Condition worsens or does not improve in 2-4 weeks.

If pregnant or breast-feeding, ask a doctor before use.
Keep out of reach of children. If swallowed, get medical help or contact a Poison Control Center right away.

Directions

Adults and children aged 12 and over.

- Wet skin thoroughly.
- Apply a generous amount of gel to damp skin.
- Gently massage onto affected areas in circular motions.
- Rinse thoroughly with water.
- Follow with a moisturizer or prescribed treatment as needed or as directed by your physician.

For optimal results, use daily or as recommended by your dermatologist

Children under 12 years old.

- Ask a doctor.

Other Information

• Store in a cool, dry place away from direct sunlight.
• Keep the dispenser tightly closed when not in use to maintain product quality.
• Keep out of reach of children.

Inactive ingredients

Water, Aloe Vera Leaf Juice, Glycerin, Allantoin, Chamomile Extract, Oat Amino Acids (Hydrolyzed Oat Protein), Tocopherol (Vitamin E), Panthenol, Cucumber Extract, Sodium PCA, Phenoxyethanol, Citric Acid, Licorice Extract, Calendula Officinalis Extract, Shea Butter, Jojoba Oil, Niacinamide, Sodium Hyaluronate, Witch Hazel Extract